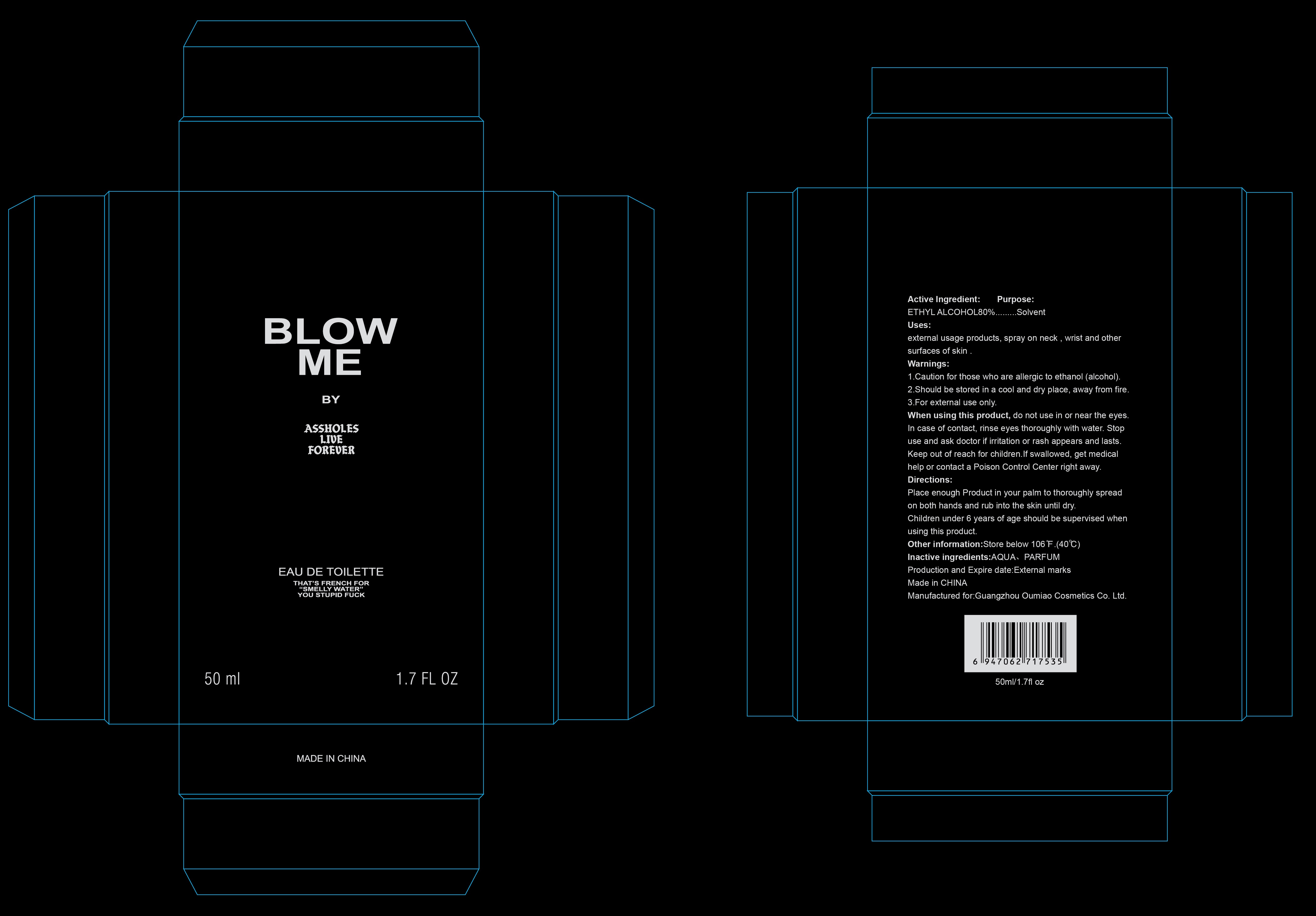 DRUG LABEL: BLOW ME
NDC: 74761-016 | Form: LIQUID
Manufacturer: Guangzhou Oumiao Cosmetics Co. Ltd. 
Category: otc | Type: HUMAN OTC DRUG LABEL
Date: 20201008

ACTIVE INGREDIENTS: ALCOHOL 80 mL/100 mL
INACTIVE INGREDIENTS: DISPERSE RED 15; WATER

74761-016
BLOW ME

Active Ingredient

ETHYL ALCOHOL80%

Purpose

Solven

Uses

external usage products, spray on neck , wrist and other surfaces of skin .

Warnings

1.Caution for those who are allergic to ethanol (alcohol).
2.Should be stored in a cool and dry place, away from fire.
3.For external use only.

When using this product, do not use in or near the eyes.
In case of contact, rinse eyes thoroughly with water. Stop use and ask doctor if irritation or rash appears and lasts.

Keep out of reach for children. If swallowed, get medical help or contact a Poison Control Center right away.

do not use in or near the eyes.
In case of contact, rinse eyes thoroughly with water.

When using this product, do not use in or near the eyes.
In case of contact, rinse eyes thoroughly with water.

Stop use and ask doctor if irritation or rash appears and lasts.

Keep out of reach for children. If swallowed, get medical help or contact a Poison Control Center right away.

Stop use and ask doctor if irritation or rash appears and lasts.

KEEP OUT OF REACH OF CHILDREN

Keep out of reach for children. If swallowed, get medical help or contact a Poison Control Center right away.

Directions

Place enough Product in your palm to thoroughly spread on both hands and rub into the skin until dry.
Children under 6 years of age should be supervised when using this product.

Other information

Store below 106°F.(40℃)

Inactive ingredients

AQUA, PARFUM